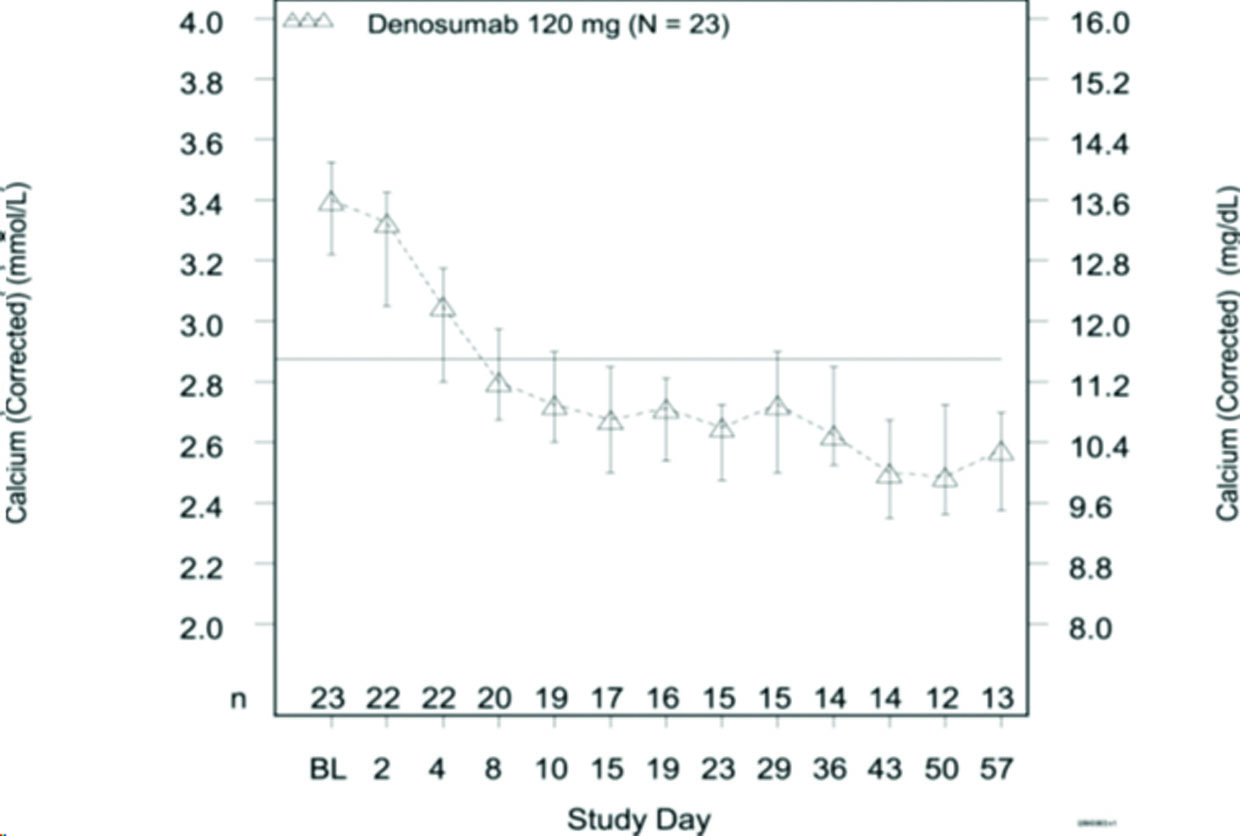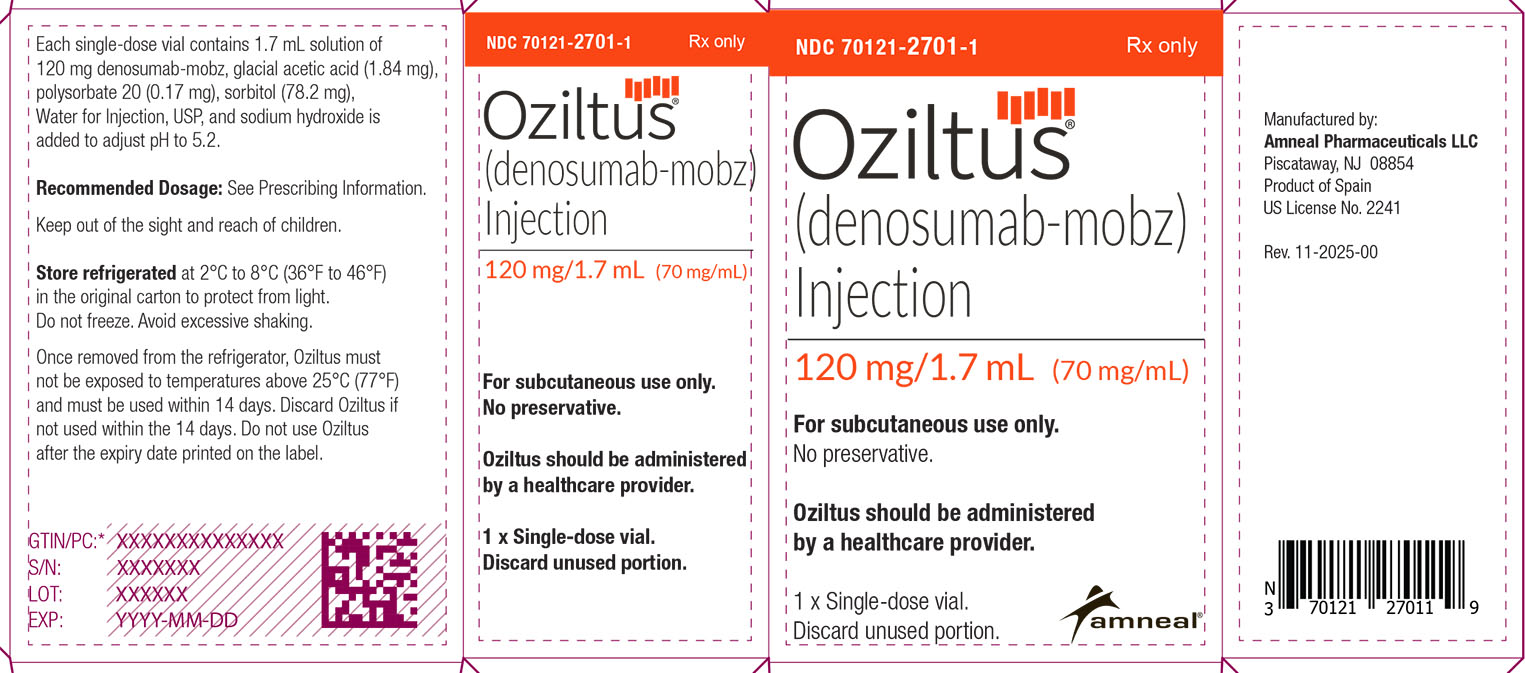 DRUG LABEL: Oziltus
NDC: 70121-2701 | Form: INJECTION, SOLUTION
Manufacturer: Amneal Pharmaceuticals LLC
Category: prescription | Type: HUMAN PRESCRIPTION DRUG LABEL
Date: 20251222

ACTIVE INGREDIENTS: DENOSUMAB 70 mg/1 mL
INACTIVE INGREDIENTS: ACETIC ACID; POLYSORBATE 20; SORBITOL SOLUTION; WATER; SODIUM HYDROXIDE

HIGHLIGHTS OF PRESCRIBING INFORMATION

These highlights do not include all the information needed to use OZILTUS safely and effectively. See full prescribing information for OZILTUS.
OZILTUS® (denosumab-mobz) injection, for subcutaneous use
Initial U.S. Approval: 2010
OZILTUS (denosumab-mobz) is biosimilar* to XGEVA® (denosumab)

1 INDICATIONS AND USAGE

Oziltus is a RANK ligand (RANKL) inhibitor indicated for:

- Prevention of skeletal-related events in patients with multiple myeloma and in patients with bone metastases from solid tumors. (1.1)
- Treatment of adults and skeletally mature adolescents with giant cell tumor of bone that is unresectable or where surgical resection is likely to result in severe morbidity. (1.2, 14.3)
- Treatment of hypercalcemia of malignancy refractory to bisphosphonate therapy. (1.3)

2 DOSAGE AND ADMINISTRATION

- Oziltus should be administered by a healthcare provider. (2.1)
- Oziltus is intended for subcutaneous route only and should not be administered intravenously, intramuscularly, or intradermally. (2.1)
- Multiple Myeloma and Bone Metastasis from Solid Tumors: Administer 120 mg every 4 weeks as a subcutaneous injection in the upper arm, upper thigh, or abdomen. (2.2)
- Giant Cell Tumor of Bone: Administer 120 mg every 4 weeks with additional 120 mg doses on Days 8 and 15 of the first month of therapy. Administer subcutaneously in the upper arm, upper thigh, or abdomen. (2.3)
- Administer calcium and vitamin D as necessary to treat or prevent hypocalcemia. (2.2, 2.3)
- Hypercalcemia of Malignancy: Administer 120 mg every 4 weeks with additional 120 mg doses on Days 8 and 15 of the first month of therapy. Administer subcutaneously in the upper arm, upper thigh, or abdomen. (2.4)

3 DOSAGE FORMS AND STRENGTHS

- Injection: 120 mg/1.7 mL (70 mg/mL) solution in a single-dose vial (3)

4 CONTRAINDICATIONS

- Hypocalcemia (4.1)
- Known clinically significant hypersensitivity to denosumab products (4.2)

5 WARNINGS AND PRECAUTIONS

- Same Active Ingredient: Patients receiving Oziltus should not take other denosumab products concomitantly. (5.1)
- Hypersensitivity reactions including anaphylaxis may occur. Discontinue permanently if a clinically significant reaction occurs. (5.2)
- Hypocalcemia: Oziltus can cause severe symptomatic hypocalcemia, and fatal cases have been reported. Correct hypocalcemia prior to initiating Oziltus. Monitor calcium levels during therapy, especially in the first weeks of initiating therapy, and adequately supplement all patients with calcium and vitamin D. (5.3)
- Osteonecrosis of the jaw (ONJ) has been reported in patients receiving denosumab products. Perform an oral examination prior to starting Oziltus. Monitor for symptoms. Avoid invasive dental procedures during treatment with Oziltus. (5.4)
- Atypical femoral fracture: Evaluate patients with thigh or groin pain to rule out a femoral fracture. (5.5)
- Hypercalcemia Following Treatment Discontinuation in Patients with Giant Cell Tumor of Bone and in Patients with Growing Skeletons: Monitor patients for signs and symptoms of hypercalcemia, and manage as clinically appropriate. (5.6, 8.4)
- Multiple Vertebral Fractures (MVF) Following Treatment Discontinuation: When Oziltus treatment is discontinued, evaluate the individual patient’s risk for vertebral fractures. (5.7)
- Embryo-Fetal Toxicity: Can cause fetal harm. Advise females of reproductive potential of potential risk to the fetus and to use effective contraception. (5.8, 8.1, 8.3)

6 ADVERSE REACTIONS

- Bone Metastasis from Solid Tumors: Most common adverse reactions (≥ 25%) were fatigue/asthenia, hypophosphatemia, and nausea. (6.1)
- Multiple Myeloma: Most common adverse reactions (≥ 10%) were diarrhea, nausea, anemia, back pain, thrombocytopenia, peripheral edema, hypocalcemia, upper respiratory tract infection, rash, and headache. (6.1)
- Giant Cell Tumor of Bone: Most common adverse reactions (≥ 10%) were arthralgia, headache, nausea, back pain, fatigue, and pain in extremity. (6.1)
- Hypercalcemia of Malignancy: Most common adverse reactions (> 20%) were nausea, dyspnea, decreased appetite, headache, peripheral edema, vomiting, anemia, constipation, and diarrhea. (6.1)

To report SUSPECTED ADVERSE REACTIONS, contact Amneal Pharmaceuticals LLC at 1-877-835-5472 or FDA at 1-800-FDA-1088 or www.fda.gov/medwatch.

8 USE IN SPECIFIC POPULATIONS

- Pediatric patients: Recommended only for treatment of skeletally mature adolescents with giant cell tumor of bone. (8.4)
- Renal impairment: Patients with creatinine clearance less than 30 mL/min or receiving dialysis are at risk for hypocalcemia. Adequately supplement with calcium and vitamin D. (8.6)

*Biosimilar means that the biological product is approved based on data demonstrating that it is highly similar to an FDA-approved biological product, known as a reference product, and that there are no clinically meaningful differences between the biosimilar product and the reference product. Biosimilarity of OZILTUS has been demonstrated for the condition(s) of use (e.g., indication(s), dosing regimen(s), strength(s), dosage form(s), and route(s) of administration described in its Full Prescribing Information.

FULL PRESCRIBING INFORMATION

1 INDICATIONS AND USAGE

1.1 Multiple Myeloma and Bone Metastasis from Solid Tumors

Oziltus is indicated for the prevention of skeletal-related events in patients with multiple myeloma and in patients with bone metastases from solid tumors.

1.2 Giant Cell Tumor of Bone

Oziltus is indicated for the treatment of adults and skeletally mature adolescents with giant cell tumor of bone that is unresectable or where surgical resection is likely to result in severe morbidity [see Clinical Trials (14.2)].

1.3 Hypercalcemia of Malignancy

Oziltus is indicated for the treatment of hypercalcemia of malignancy refractory to bisphosphonate therapy.

2 DOSAGE AND ADMINISTRATION

2.1 Important Administration Instructions

Oziltus should be administered by a healthcare provider.

Oziltus is intended for subcutaneous route only and should not be administered intravenously, intramuscularly, or intradermally.

2.2 Multiple Myeloma and Bone Metastasis from Solid Tumors

The recommended dose of Oziltus is 120 mg administered as a subcutaneous injection every 4 weeks in the upper arm, upper thigh, or abdomen.

Administer calcium and vitamin D as necessary to treat or prevent hypocalcemia [see Warnings and Precautions (5.3)].

2.3 Giant Cell Tumor of Bone

The recommended dose of Oziltus is 120 mg administered every 4 weeks with additional 120 mg doses on Days 8 and 15 of the first month of therapy. Administer subcutaneously in the upper arm, upper thigh, or abdomen.

Administer calcium and vitamin D as necessary to treat or prevent hypocalcemia [see Warnings and Precautions (5.3)].

2.4 Hypercalcemia of Malignancy

The recommended dose of Oziltus is 120 mg administered every 4 weeks with additional 120 mg doses on Days 8 and 15 of the first month of therapy. Administer subcutaneously in the upper arm, upper thigh, or abdomen.

2.5 Preparation and Administration

Parenteral drug products should be inspected visually for particulate matter and discoloration prior to administration whenever solution and container permit. Oziltus is a clear, colorless to pale yellow solution. Do not use if the solution is discolored or cloudy or if the solution contains visible particles or foreign particulate matter.

Prior to administration, Oziltus may be removed from the refrigerator and brought to room temperature up to 25°C (77°F) by standing in the original container. This generally takes 15 to 30 minutes. Do not warm Oziltus in any other way [see How Supplied/Storage and Handling (16)].

Use a 27-gauge needle to withdraw and inject the entire contents of the vial. Do not re-enter the vial. Discard vial after single entry.

3 DOSAGE FORMS AND STRENGTHS

Injection: 120 mg/1.7 mL (70 mg/mL) clear, colorless to pale yellow solution in a single-dose vial.

4 CONTRAINDICATIONS

4.1 Hypocalcemia

Pre-existing hypocalcemia must be corrected prior to initiating therapy with Oziltus [see Warnings and Precautions (5.3)].

4.2 Hypersensitivity

Oziltus is contraindicated in patients with known clinically significant hypersensitivity to denosumab products [see Warnings and Precautions (5.2) and Adverse Reactions (6.2)].

5 WARNINGS AND PRECAUTIONS

5.1 Drug Products with Same Active Ingredient

Patients receiving Oziltus should not receive other denosumab products concomitantly.

5.2 Hypersensitivity

Clinically significant hypersensitivity including anaphylaxis has been reported with use of denosumab products. Reactions may include hypotension, dyspnea, upper airway edema, lip swelling, rash, pruritus, and urticaria. If an anaphylactic or other clinically significant allergic reaction occurs, initiate appropriate therapy and discontinue Oziltus therapy permanently [see Contraindications (4.2) and Adverse Reactions (6.2)].

5.3 Hypocalcemia

Denosumab products can cause severe symptomatic hypocalcemia, and fatal cases have been reported. Correct pre-existing hypocalcemia prior to Oziltus treatment. Monitor calcium levels, throughout Oziltus therapy, especially in the first weeks of initiating therapy, and administer calcium, magnesium, and vitamin D as necessary. Concomitant use of calcimimetics and other drugs that can lower calcium levels may worsen hypocalcemia risk and serum calcium should be closely monitored. Advise patients to contact a healthcare provider for symptoms of hypocalcemia [see Contraindications (4.1), Adverse Reactions (6.1, 6.2), and Patient Counseling Information (17)].

An increased risk of hypocalcemia has been observed in clinical trials of patients with increasing renal dysfunction, most commonly with severe dysfunction (creatinine clearance less than 30 mL/min and/or on dialysis), and with inadequate/no calcium supplementation. Monitor calcium levels and calcium and vitamin D intake [see Adverse Reactions (6.1), Use in Specific Populations (8.6), and Clinical Pharmacology (12.3)].

5.4 Osteonecrosis of the Jaw (ONJ)

Osteonecrosis of the jaw (ONJ) has been reported in patients receiving denosumab products, manifesting as jaw pain, osteomyelitis, osteitis, bone erosion, tooth or periodontal infection, toothache, gingival ulceration, or gingival erosion. Persistent pain or slow healing of the mouth or jaw after dental surgery may also be manifestations of ONJ. In clinical trials in patients with cancer, the incidence of ONJ was higher with longer duration of exposure [see Adverse Reactions (6.1)]. Seventy-nine percent of patients with ONJ had a history of tooth extraction, poor oral hygiene, or use of a dental appliance as a predisposing factor. Other risk factors for the development of ONJ include immunosuppressive therapy, treatment with angiogenesis inhibitors, systemic corticosteroids, diabetes, and gingival infections. Similarly, for denosumab-treated patients with multiple myeloma that developed ONJ, 58% had a history of invasive dental procedures as a predisposing factor.

Perform an oral examination and appropriate preventive dentistry prior to the initiation of Oziltus and periodically during Oziltus therapy. Advise patients regarding oral hygiene practices. Avoid invasive dental procedures during treatment with Oziltus. Consider temporary discontinuation of Oziltus therapy if an invasive dental procedure must be performed. There are no data available to suggest the optimal duration of treatment interruption.

Patients who are suspected of having or who develop ONJ while on Oziltus should receive care by a dentist or an oral surgeon. In these patients, extensive dental surgery to treat ONJ may exacerbate the condition. Clinical judgment of the treating healthcare provider should guide the management plan of each patient based on individual risk/benefit assessment.

5.5 Atypical Subtrochanteric and Diaphyseal Femoral Fracture

Atypical femoral fracture has been reported with denosumab products [see Adverse Reactions (6.1)]. These fractures can occur anywhere in the femoral shaft from just below the lesser trochanter to above the supracondylar flare and are transverse or short oblique in orientation without evidence of comminution.

Atypical femoral fractures most commonly occur with minimal or no trauma to the affected area. They may be bilateral and many patients report prodromal pain in the affected area, usually presenting as dull, aching thigh pain, weeks to months before a complete fracture occurs. A number of reports note that patients were also receiving treatment with glucocorticoids (e.g. prednisone) at the time of fracture.

During Oziltus treatment, patients should be advised to report new or unusual thigh, hip, or groin pain. Any patient who presents with thigh or groin pain should be suspected of having an atypical fracture and should be evaluated to rule out an incomplete femur fracture. Patient presenting with an atypical femur fracture should also be assessed for symptoms and signs of fracture in the contralateral limb. Interruption of Oziltus therapy should be considered, pending a risk/benefit assessment, on an individual basis.

5.6 Hypercalcemia Following Treatment Discontinuation in Patients with Giant Cell Tumor of Bone and in Patients with Growing Skeletons

Clinically significant hypercalcemia requiring hospitalization and complicated by acute renal injury has been reported in denosumab product-treated patients with giant cell tumor of bone and patients with growing skeletons. Hypercalcemia has been reported within the first year after treatment discontinuation. After treatment is discontinued, monitor patients for signs and symptoms of hypercalcemia, assess serum calcium periodically, reevaluate the patient’s calcium and vitamin D supplementation requirements and manage patients as clinically appropriate [see Adverse Reactions (6) and Use in Specific Populations (8.4)].

5.7 Multiple Vertebral Fractures (MVF) Following Treatment Discontinuation

Multiple vertebral fractures (MVF) have been reported following discontinuation of treatment with denosumab products. Patients at higher risk for MVF include those with risk factors for or a history of osteoporosis or prior fractures.

When Oziltus treatment is discontinued, evaluate the individual patient’s risk for vertebral fractures [see Patient Counseling Information (17)].

5.8 Embryo-Fetal Toxicity

Based on data from animal studies and its mechanism of action, denosumab products can cause fetal harm when administered to a pregnant woman. In animal reproduction studies, administration of denosumab to cynomolgus monkeys throughout pregnancy at a dose 25-fold higher than the recommended human dose of denosumab based on body weight resulted in increased fetal loss, stillbirths, and postnatal mortality, along with evidence of absent peripheral lymph nodes, abnormal bone growth and decreased neonatal growth.

Verify the pregnancy status of females of reproductive potential prior to the initiation of Oziltus. Advise pregnant women and females of reproductive potential that exposure to Oziltus during pregnancy or within 5 months prior to conception can result in fetal harm. Advise females of reproductive potential to use effective contraception during therapy, and for at least 5 months after the last dose of Oziltus [see Use in Specific Populations (8.1, 8.3) and Clinical Pharmacology (12.1)].

6 ADVERSE REACTIONS

The following adverse reactions are discussed below and elsewhere in the labeling:

- Hypersensitivity [see Warnings and Precautions (5.2)]
- Hypocalcemia [see Warnings and Precautions (5.3) and Use in Specific Populations (8.6)]
- Osteonecrosis of the Jaw [see Warnings and Precautions (5.4)]
- Atypical Subtrochanteric and Diaphyseal Femoral Fracture [see Warnings and Precautions (5.5)]
- Hypercalcemia following treatment discontinuation in patients with giant cell tumor of bone and in patients with growing skeletons [see Warnings and Precautions (5.6) and Use in Specific Populations (8.4)]
- Multiple vertebral fractures (MVF) following treatment discontinuation [see Warnings and Precautions (5.7)]

6.1 Clinical Trials Experience

Because clinical trials are conducted under widely varying conditions, adverse reaction rates observed in the clinical trials of a drug cannot be directly compared to rates in the clinical trials of another drug and may not reflect the rates observed in practice.

Bone Metastasis from Solid Tumors

The safety of denosumab was evaluated in three randomized, double-blind, double-dummy trials [see Clinical Trials (14.1)] in which a total of 2841 patients with bone metastasis from prostate cancer, breast cancer, or other solid tumors, or lytic bony lesions from multiple myeloma received at least one dose of denosumab. In Studies 20050136, 20050244, and 20050103, patients were randomized to receive either 120 mg of denosumab every 4 weeks as a subcutaneous injection or 4 mg (dose adjusted for reduced renal function) of zoledronic acid every 4 weeks by intravenous (IV) infusion. Entry criteria included serum calcium (corrected) from 8 to 11.5 mg/dL (2 to 2.9 mmol/L) and creatinine clearance 30 mL/min or greater. Patients who had received IV bisphosphonates were excluded, as were patients with prior history of ONJ or osteomyelitis of the jaw, an active dental or jaw condition requiring oral surgery, non-healed dental/oral surgery, or any planned invasive dental procedure. During the study, serum chemistries including calcium and phosphorus were monitored every 4 weeks. Calcium and vitamin D supplementation was recommended but not required.

The median duration of exposure to denosumab was 12 months (range: 0.1 to 41) and median duration on-study was 13 months (range: 0.1 to 41). Of patients who received denosumab, 46% were female. Eighty-five percent were White, 5% Hispanic/Latino, 6% Asian, and 3% Black. The median age was 63 years (range: 18 to 93). Seventy-five percent of patients who received denosumab received concomitant chemotherapy.

The most common adverse reactions in patients (incidence greater than or equal to 25%) were fatigue/asthenia, hypophosphatemia, and nausea (see Table 1). The most common serious adverse reaction was dyspnea. The most common adverse reactions resulting in discontinuation of denosumab were osteonecrosis and hypocalcemia.

Table 1. Selecteda Adverse Reactions of Any Severity (Studies 20050136, 20050244, and 20050103)

Body System | Denosumab; n = 2841; % | Zoledronic Acid; n = 2836; %
GASTROINTESTINAL
Nausea | 31 | 32
Diarrhea | 20 | 19
GENERAL
Fatigue/Asthenia | 45 | 46
INVESTIGATIONS
Hypocalcemiab | 18 | 9
Hypophosphatemiab | 32 | 20
NEUROLOGICAL
Headache | 13 | 14
RESPIRATORY
Dyspnea | 21 | 18
Cough | 15 | 15

a Adverse reactions reported in at least 10% of patients receiving denosumab in Studies 20050136, 20050244, and 20050103, and meeting one of the following criteria:

- At least 1% greater incidence in denosumab-treated patients, or
- Between-group difference (either direction) of less than 1% and more than 5% greater incidence in patients treated with zoledronic acid compared to placebo (US Prescribing Information for zoledronic acid)

b Laboratory-derived and below the central laboratory lower limit of normal [8.3 to 8.5 mg/dL (2.075 to 2.125 mmol/L) for calcium and 2.2 to 2.8 mg/dL (0.71 to 0.9 mmol/L) for phosphorus]

Severe Mineral/Electrolyte Abnormalities

- Severe hypocalcemia (corrected serum calcium less than 7 mg/dL or less than 1.75 mmol/L) occurred in 3.1% of patients treated with denosumab and 1.3% of patients treated with zoledronic acid. Of patients who experienced severe hypocalcemia, 33% experienced 2 or more episodes of severe hypocalcemia and 16% experienced 3 or more episodes [see Warnings and Precautions (5.3) and Use in Specific Populations (8.6)].
- Severe hypophosphatemia (serum phosphorus less than 2 mg/dL or less than 0.6 mmol/L) occurred in 15.4% of patients treated with denosumab and 7.4% of patients treated with zoledronic acid.

Osteonecrosis of the Jaw (ONJ)

In the primary treatment phases of Studies 20050136, 20050244, and 20050103, ONJ was confirmed in 1.8% of patients in the denosumab group (median exposure of 12.0 months; range: 0.1 to 41) and 1.3% of patients in the zoledronic acid group. The trials in patients with breast (Study 20050136) or prostate (Study 20050103) cancer included an open-label extension treatment phase where patients were offered denosumab 120 mg once every 4 weeks (median overall exposure of 14.9 months; range: 0.1 to 67.2). The patient-year adjusted incidence (number of events per 100 patient years) of confirmed ONJ was 1.1% during the first year of treatment, 3.7% in the second year, and 4.6% per year thereafter. The median time to ONJ was 20.6 months (range: 4 to 53) [see Warnings and Precautions (5.4)].

In a placebo-controlled clinical trial with an extension treatment phase evaluating denosumab for the prevention of bone metastases in patients with non-metastatic prostate cancer (a patient population for which denosumab is not indicated), with longer treatment exposure of up to 7 years, the patient-year adjusted incidence (number of events per 100 patient years) of confirmed ONJ was 1.1% during the first year of treatment, 3% in the second year, and 7% per year thereafter.

Atypical Subtrochanteric and Diaphyseal Fracture

In the clinical trial program, atypical femoral fracture has been reported in patients treated with denosumab and the risk increased with longer duration of treatment. Events have occurred during treatment and after treatment was discontinued [see Warnings and Precautions (5.5)].

Multiple Myeloma

The safety of denosumab was evaluated in an international, randomized (1:1), double-blind, active-controlled trial of patients with newly diagnosed multiple myeloma with treatment through disease progression [see Clinical Trials (14.2)]. In this trial, patients received 120 mg denosumab every 4 weeks as a subcutaneous injection (n = 850) or 4 mg (dose adjusted for renal function) of zoledronic acid intravenously (IV) every 4 weeks by IV infusion (n = 852). Entry criteria included serum calcium (corrected) from 8 to 11.5 mg/dL (2 to 2.9 mmol/L) and creatinine clearance 30 mL/min or greater. Patients who had received IV bisphosphonates were excluded, as were patients with prior history of ONJ or osteomyelitis of the jaw, an active dental or jaw condition requiring oral surgery, non-healed dental/oral surgery, or any planned invasive dental procedure. During the study, serum chemistries including calcium and phosphorus were monitored every 4 weeks. Calcium and vitamin D supplementation was recommended but not required.

The median duration of exposure to denosumab was 16 months (range: 1 to 50) and median duration on-study was 17 months (range: 0 to 49). Of patients who received denosumab, 46% were female, 83% percent were White, 13% Asian, 3% Black or African American, and 4% Hispanic/Latino. The median age of the patients randomized to denosumab was 63 years (range: 29 to 91) and all patients who received denosumab received concomitant anti-myeloma chemotherapy.

The adverse reaction profile of denosumab in patients with multiple myeloma, Study 20090482, was similar to that observed in Studies 20050136, 20050244, and 20050103. The most common adverse reactions (incidence ≥ 10%) were diarrhea (34%), nausea (32%), anemia (22%), back pain (21%), thrombocytopenia (19%), peripheral edema (17%), hypocalcemia (16%), upper respiratory tract infection (15%), rash (14%), and headache (11%). The most common serious adverse reaction (incidence ≥ 5%) was pneumonia (8%). The most common adverse reaction resulting in discontinuation of denosumab (≥ 1%) was osteonecrosis of the jaw.

Hypocalcemia and Hypophosphatemia

Severe hypocalcemia (corrected serum calcium less than 7 mg/dL or less than 1.75 mmol/L) and severe hypophosphatemia (serum phosphorus less than 2 mg/dL or less than 0.6 mmol/L) occurred in 2% and 21% patients treated with denosumab, respectively.

Osteonecrosis of the Jaw (ONJ)

In the primary treatment phase of Study 20090482, ONJ was confirmed in 4.1% of patients in the denosumab group (median exposure of 16 months; range: 1 to 50) and 2.8% of patients in the zoledronic acid group (median 15 months, range: 1 to 45 months). At the completion of the double-blind treatment phase of Study 20090482, the patient-year adjusted incidence (number of events per 100 patient years) of confirmed ONJ in the denosumab group (median exposure of 19.4 months; range 1 to -52) was 2% during the first year of treatment, 5% in the second year, and 4.5% per year thereafter. The median time to ONJ was 18.7 months (range: 1 to 44) [see Warnings and Precautions (5.4)].

Giant Cell Tumor of Bone

The safety of denosumab was evaluated in two single-arm trials (Study 20062004 and Study 20040215) [see Clinical Trials (14.3)] in which a total of 548 adult or skeletally mature adolescent patients with giant cell tumor of bone received at least 1 dose of denosumab. Patients received 120 mg denosumab subcutaneously every 4 weeks with additional 120 mg doses on Days 8 and 15 of the first month of therapy. Patients receiving concurrent bisphosphonate therapy were excluded from enrollment in both studies. Patients with prior history of ONJ or osteomyelitis of the jaw, an active dental or jaw condition requiring oral surgery, non-healed dental/oral surgery, or any planned invasive dental procedure were excluded from enrollment in Study 20040215. During the trial, serum chemistries including calcium and phosphorus were monitored every 4 weeks. Calcium and vitamin D supplementation was recommended but not required.

Of the 548 patients who received denosumab, 467 patients were treated with denosumab for ≥ 1 year, 323 patients for ≥ 2 years, and 255 patients for ≥ 3 years. The median number of doses received was 33 (range: 4 to 138 doses) and the median number of months on-study was 60 (range: 0 to 140 months). Fifty-seven percent of the enrolled patients were women and 82% were White. The median age was 33 years (range: 13 to 83 years); a total of 19 patients were skeletally mature adolescents (12 to ≤ 17 years of age).

The common adverse reaction profile of denosumab in patients with giant cell tumor of bone was generally similar to that reported in Studies 20050136, 20050244, and 20050103. The most common adverse reactions in patients (incidence ≥ 10%) were arthralgia, back pain, pain in extremity, fatigue, headache, nausea, nasopharyngitis, musculoskeletal pain, toothache, vomiting, hypophosphatemia, constipation, diarrhea, and cough. The most frequent serious adverse reactions were osteonecrosis of the jaw (3.6%), bone giant cell tumor (1.5%), anemia (1.1%), pneumonia (0.9%), and back pain (0.9%). The most frequent adverse reactions resulting in discontinuation of denosumab was osteonecrosis of the jaw (incidence of 3.6%). The adverse reaction profile appeared similar in skeletally mature adolescents and adults.

Hypocalcemia and Hypophosphatemia

- Moderate to severe hypocalcemia (corrected serum calcium less than 8 mg/dL or less than 2 mmol/L) occurred in 5% of patients treated with denosumab.
- Severe hypophosphatemia (serum phosphorus less than 2 to 1 mg/dL or less than 0.6 to 0.3 mmol/L) occurred in 20% of patients treated with denosumab.

Osteonecrosis of the Jaw (ONJ)

In the pooled analysis of Study 20062004 and Study 20040215, ONJ was confirmed in 7% of patients who received denosumab (median number of doses received: 33; range: 4 to 138 doses).

Study 20140114 (NCT03301857) was a 5-year long term follow-up study for patients (n = 85) who completed Study 20062004. In Study 20062004 and Study 20140114 combined, ONJ was confirmed in 7% of patients who received denosumab (median time on trial 62.2 months (range 0-173). The combined patient-year adjusted incidence (number of events per 100 patient years) of confirmed ONJ was 0.2% during the first year of treatment, 1.5% in the second year, 1.8% in the third year, 2.1% in the fourth year, 1.4% in the fifth year, and 1.5% thereafter [see Warnings and Precautions (5.4)].

Atypical Subtrochanteric and Diaphyseal Fracture

In the pooled analysis of Study 20062004 and Study 20040215, atypical femoral fracture was observed in 0.9% of patients who received denosumab (median number of doses received: 33; range: 4-138 doses).

In Study 20062004 and Study 20140114, the combined incidence of confirmed atypical femoral fracture was 1.3% of patients who received denosumab [see Warnings and Precautions (5.5)].

Hypercalcemia Following Treatment Discontinuation

In the pooled safety population, 0.7% of patients experienced serious adverse events of hypercalcemia > 30 days following treatment discontinuation that was recurrent in some patients [see Warnings and Precautions (5.6)].

Hypercalcemia of Malignancy

Denosumab was evaluated in an open-label, single-arm trial (Study 20070315) in which 33 patients with hypercalcemia of malignancy (with or without bone metastases) refractory to treatment with intravenous bisphosphonate therapy were enrolled [see Clinical Trials (14.4)].

The adverse reaction profile of denosumab in patients with hypercalcemia of malignancy was similar to that reported in Studies 20050136, 20050244, 20050103, 20062004, and 20040215. Adverse reactions occurring in greater than 20% of patients were nausea (30%), dyspnea (27%), decreased appetite (24%), headache (24%), peripheral edema (24%), vomiting (24%), anemia (21%), constipation (21%), and diarrhea (21%). The following adverse reactions of Grade 3 or greater severity related to study therapy were reported on-study: fatigue (3%) and infection (6%). Grade 3 laboratory abnormalities included hypomagnesemia (3%), hypokalemia (3%), and hypophosphatemia (76%) of patients. No deaths on-study were related to denosumab therapy.

6.2 Postmarketing Experience

The following adverse reactions have been identified during post approval use of denosumab products. Because these reactions are reported voluntarily from a population of uncertain size, it is not always possible to reliably estimate their frequency or establish a causal relationship to drug exposure.

- Hypocalcemia: Severe symptomatic hypocalcemia, including fatal cases [see Contraindications (4.1) and Warnings and Precautions (5.3)].
- Hypercalcemia: Severe symptomatic hypercalcemia following treatment discontinuation can occur [see Adverse Reactions (6) and Warnings and Precautions (5.6)].
- Hypersensitivity, including anaphylactic reactions [see Contraindications (4.2) and Warnings and Precautions (5.2)].
- Musculoskeletal pain, including severe musculoskeletal pain. Positive re-challenge has been reported.
- Lichenoid drug eruptions (e.g., lichen planus-like reactions).
- Alopecia.

8 USE IN SPECIFIC POPULATIONS

8.1 Pregnancy

Risk Summary

Based on findings in animals and its mechanism of action, denosumab products can cause fetal harm when administered to a pregnant woman [see Clinical Pharmacology (12.1)]. There are insufficient data with denosumab products use in pregnant women to inform any drug associated risks for adverse developmental outcomes. In utero denosumab exposure from cynomolgus monkeys dosed monthly with denosumab throughout pregnancy at a dose 25-fold higher than the recommended human dose of denosumab based on body weight resulted in increased fetal loss, stillbirths, and postnatal mortality; and absent lymph nodes, abnormal bone growth, and decreased neonatal growth [see Data].

Apprise pregnant women of the potential risk to the fetus.

The background rate of major birth defects and miscarriage is unknown for the indicated population. In the U.S. general population, the estimated background risk of major birth defects and miscarriage in clinically recognized pregnancies is 2% to 4% and 15% to 20%, respectively.

Data

Animal Data

The effects of denosumab on prenatal development have been studied in both cynomolgus monkeys and genetically engineered mice in which RANK ligand (RANKL) expression was turned off by gene removal (a “knockout mouse”). In cynomolgus monkeys dosed subcutaneously with denosumab throughout pregnancy starting at gestational day 20 and at a pharmacologically active dose 25-fold higher than the recommended human dose of denosumab based on body weight, there was increased fetal loss during gestation, stillbirths, and postnatal mortality. Other findings in offspring included absence of axillary, inguinal, mandibular, and mesenteric lymph nodes; abnormal bone growth, reduced bone strength, reduced hematopoiesis, dental dysplasia, and tooth malalignment; and decreased neonatal growth. At birth out to one month of age, infants had measurable blood levels of denosumab (22% to 621% of maternal levels).

Following a recovery period from birth out to 6 months of age, the effects on bone quality and strength returned to normal; there were no adverse effects on tooth eruption, though dental dysplasia was still apparent; axillary and inguinal lymph nodes remained absent, while mandibular and mesenteric lymph nodes were present, though small; and minimal to moderate mineralization in multiple tissues was seen in one recovery animal. There was no evidence of maternal harm prior to labor; adverse maternal effects occurred infrequently during labor. Maternal mammary gland development was normal. There was no fetal NOAEL (no observable adverse effect level) established for this study because only one dose of 50 mg/kg was evaluated. Mammary gland histopathology at 6 months of age was normal in female offspring exposed to denosumab in utero; however, development and lactation have not been fully evaluated.

In RANKL knockout mice, absence of RANKL (the target of denosumab) also caused fetal lymph node agenesis and led to postnatal impairment of dentition and bone growth. Pregnant RANKL knockout mice showed altered maturation of the maternal mammary gland, leading to impaired lactation [see Use in Specific Populations (8.3) and Nonclinical Toxicology (13.2)].

8.2 Lactation

Risk Summary

There is no information regarding the presence of denosumab products in human milk, the effects on the breastfed child, or the effects on milk production. Denosumab was detected in the maternal milk of cynomolgus monkeys up to 1 month after the last dose of denosumab (≤ 0.5% milk:serum ratio) and maternal mammary gland development was normal, with no impaired lactation. However, pregnant RANKL knockout mice showed altered maturation of the maternal mammary gland, leading to impaired lactation [see Use in Specific Populations (8.1) and Nonclinical Toxicology (13.2)]. Consider the developmental and health benefits of breastfeeding along with the mother’s clinical need for Oziltus treatment and any potential adverse effects on the breastfed child from Oziltus or from the underlying maternal condition.

8.3 Females and Males of Reproductive Potential

Based on findings in animals and its mechanism of action, denosumab products can cause fetal harm when administered to a pregnant woman [see Use in Specific Populations (8.1)].

Pregnancy Testing

Verify the pregnancy status of females of reproductive potential prior to initiating Oziltus treatment.

Contraception

Females

Advise females of reproductive potential to use effective contraception during therapy, and for at least 5 months after the last dose of Oziltus.

8.4 Pediatric Use

The safety and efficacy of Oziltus have not been established in pediatric patients except in skeletally mature adolescents (aged 12 to 16 years) with giant cell tumor of bone. Oziltus is recommended only for treatment of skeletally mature adolescents (aged 12 to 16 years) with giant cell tumor of bone [see Indications and Usage (1.2)]. Clinically significant hypercalcemia after treatment discontinuation has been reported in pediatric patients with growing skeletons who received denosumab products for giant cell tumor of bone or for unapproved indications [see Adverse Reactions (6.2) and Warnings and Precautions (5.6)].

Denosumab was studied in an open-label trial that enrolled a subset of 19 adolescent patients (aged 12 to 16 years) with giant cell tumor of bone who had reached skeletal maturity, defined by at least 1 mature long bone (e.g., closed epiphyseal growth plate of the humerus), and had a body weight ≥ 45 kg [see Indications and Usage (1.2) and Clinical Trials (14.3)]. A total of one of five (20%) evaluable adolescent patients had an objective response by retrospective independent assessment of radiographic response according to modified Response Evaluation Criteria in Solid Tumors (RECIST 1.1). The adverse reaction profile and efficacy results appeared to be similar in skeletally mature adolescents and adults [see Adverse Reactions (6.1) and Clinical Trials (14.3)].

Animal Data

Treatment with denosumab products may impair bone growth in children with open growth plates and may inhibit eruption of dentition. In neonatal rats, inhibition of RANKL (the target of denosumab therapy) with a construct of osteoprotegerin bound to Fc (OPG-Fc) at doses ≤ 10 mg/kg was associated with inhibition of bone growth and tooth eruption. Adolescent primates treated with denosumab at doses 5 and 25 times (10 and 50 mg/kg dose) higher than the recommended human dose of 120 mg administered once every 4 weeks, based on body weight (mg/kg), had abnormal growth plates, considered to be consistent with the pharmacological activity of denosumab.

Cynomolgus monkeys exposed in utero to denosumab exhibited bone abnormalities, reduced hematopoiesis, tooth malalignment, decreased neonatal growth, and an absence of axillary, inguinal, mandibular, and mesenteric lymph nodes. Some bone abnormalities recovered once exposure was ceased following birth; however, axillary and inguinal lymph nodes remained absent 6 months post-birth [see Use in Specific Populations (8.1)].

8.5 Geriatric Use

Of the total number of patients in clinical studies that received denosumab (n = 2841) in Studies 20050136, 20050244, and 20050103, 1271 (44%) were ≥ 65 years old, while 473 patients (17%) were ≥ 75 years old. Of the 859 patients in Study 20090482 that received denosumab, 387 patients (45%) were ≥ 65 years old, while 141 patients (16%) were ≥ 75 years old. No overall differences in safety or efficacy were observed between older and younger patients.

8.6 Renal Impairment

Two clinical trials were conducted in patients without cancer and with varying degrees of renal function.

In one study, patients (N = 55) with varying degrees of renal function (ranging from normal through end-stage renal disease requiring dialysis) received a single 60 mg subcutaneous dose of denosumab. In a second study, patients (N = 32) with severe renal dysfunction (creatinine clearance less than 30 mL/min and/or on dialysis) were given two 120 mg subcutaneous doses of denosumab. In both studies, greater risk of developing hypocalcemia was observed with increasing renal impairment, and with inadequate/no calcium supplementation. Hypocalcemia was mild to moderate in severity in 96% of patients. Monitor calcium levels and calcium and vitamin D intake [see Warnings and Precautions (5.3), Adverse Reactions (6.1), and Clinical Pharmacology (12.3)].

10 OVERDOSAGE

There is no experience with overdosage of denosumab products.

11 DESCRIPTION

Denosumab-mobz is a human IgG2 monoclonal antibody that binds to human RANKL. Denosumab has an approximate molecular weight of 147 kDa and is produced in genetically engineered mammalian (Chinese hamster ovary) cells.

Oziltus (denosumab-mobz) is a sterile, preservative-free, clear, colorless to pale yellow solution.

Each single-dose vial contains 1.7 mL solution of 120 mg denosumab, glacial acetic acid (1.84 mg), polysorbate 20 (0.17 mg), sorbitol (78.20 mg), Water for Injection (USP), and sodium hydroxide to a pH of 5.2.

12 CLINICAL PHARMACOLOGY

12.1 Mechanism of Action

Denosumab products bind to RANKL, a transmembrane or soluble protein essential for the formation, function, and survival of osteoclasts, the cells responsible for bone resorption, thereby modulating calcium release from bone. Increased osteoclast activity, stimulated by RANKL, is a mediator of bone pathology in solid tumors with osseous metastases. Similarly, giant cell tumors of bone consist of stromal cells expressing RANKL and osteoclast-like giant cells expressing RANK receptor, and signaling through the RANK receptor contributes to osteolysis and tumor growth. Denosumab products prevent RANKL from activating its receptor, RANK, on the surface of osteoclasts, their precursors, and osteoclast-like giant cells.

12.2 Pharmacodynamics

In patients with breast cancer and bone metastases, the median reduction in uNTx/Cr was 82% within 1 week following initiation of denosumab 120 mg administered subcutaneously. In Studies 20050136, 20050244, and 20050103, the median reduction in uNTx/Cr from baseline to Month 3 was approximately 80% in 2075 denosumab-treated patients.

In a phase 3 study of patients with newly diagnosed multiple myeloma who received subcutaneous doses of denosumab 120 mg every 4 weeks (Q4W), median reductions in uNTx/Cr of approximately 75% were observed by Week 5. Reductions in bone turnover markers were maintained, with median reductions of 74% to 79% for uNTx/Cr from weeks 9 to 49 of continued 120 mg Q4W dosing.

In adult and skeletally mature adolescent patients with giant cell tumor of bone who received subcutaneous doses of denosumab 120 mg Q4W with a 120 mg loading dose on Days 8 and 15, median reductions in uNTx/Cr from baseline were 84% at Week 13 and 82% at Week 25.

12.3 Pharmacokinetics

Following subcutaneous administration, bioavailability was 62%. Denosumab displayed nonlinear pharmacokinetics at doses below 60 mg, but approximately dose-proportional increases in exposure at higher doses.

With multiple subcutaneous doses of 120 mg once every 4 weeks, up to 2.8-fold accumulation in serum denosumab concentrations was observed and steady-state was achieved by 6 months. A mean (± standard deviation) serum steady-state trough concentration of 20.5 (± 13.5) mcg/mL was achieved by 6 months. The mean elimination half-life was 28 days.

In patients with newly diagnosed multiple myeloma who received 120 mg every 4 weeks, denosumab concentrations appear to reach steady-state by Month 6. In patients with giant cell tumor of bone, after administration of subcutaneous doses of 120 mg once every 4 weeks with additional 120 mg doses on Days 8 and 15 of the first month of therapy, mean (± standard deviation) serum trough concentrations on Day 8, 15, and one month after the first dose were 19.0 (± 24.1), 31.6 (± 27.3), 36.4 (± 20.6) mcg/mL, respectively. Steady-state was achieved in 3 months after initiation of treatment with a mean serum trough concentration of 23.4 (± 12.1) mcg/mL.

Special Populations

Body Weight: A population pharmacokinetic analysis was performed to evaluate the effects of demographic characteristics. Denosumab clearance and volume of distribution were proportional to body weight. The steady-state exposure following repeat subcutaneous administration of 120 mg every 4 weeks to 45 kg and 120 kg subjects were, respectively, 48% higher and 46% lower than exposure of the typical 66 kg subject.

Age, Gender and Race: The pharmacokinetics of denosumab was not affected by age, gender, and race.

Pediatrics: In skeletally-mature adolescent patients (12 to 16 years of age) with giant cell tumor of bone (GCTB) who received 120 mg every 4 weeks with a 120 mg loading dose on Days 8 and 15, the pharmacokinetics of denosumab were comparable to those observed in adult patients with GCTB.

Hepatic Impairment: No clinical trials have been conducted to evaluate the effect of hepatic impairment on the pharmacokinetics of denosumab products.

Renal Impairment: In clinical trials of 87 patients with varying degrees of renal dysfunction, including patients on dialysis, the degree of renal impairment had no effect on the pharmacokinetics and pharmacodynamics of denosumab [see Use in Specific Populations (8.6)].

Drug Interactions

No formal drug-drug interaction trials have been conducted with denosumab. There was no evidence that various anticancer treatments affected denosumab systemic exposure and pharmacodynamic effect. Serum denosumab concentrations at 1 and 3 months and reductions in the bone turnover marker uNTx/Cr (urinary N-terminal telopeptide corrected for creatinine) at 3 months were similar in patients with and without prior intravenous bisphosphonate therapy and were not altered by concomitant chemotherapy and/or hormone therapy.

12.6 Immunogenicity

The observed incidence of anti-drug antibodies is highly dependent on the sensitivity and specificity of the assay. Differences in assay methods preclude meaningful comparisons of the incidence of anti-drug antibodies in the studies described below with the incidence of anti-drug antibodies in other studies, including those of denosumab or of other denosumab products.

Using an electrochemiluminescent bridging immunoassay, less than 1% (55 out of 8113) of patients treated with denosumab for up to 5 years tested positive for binding antibodies (including pre-existing, transient, and developing antibodies). None of the patients tested positive for neutralizing antibodies, as was assessed using a chemiluminescent cell-based in vitro biological assay. There was no identified clinically significant effect of anti-drug antibodies on pharmacokinetics, pharmacodynamics, safety, or effectiveness of denosumab.

13 NONCLINICAL TOXICOLOGY

13.1 Carcinogenesis, Mutagenesis, Impairment of Fertility

Carcinogenicity

The carcinogenic potential of denosumab products has not been evaluated in long-term animal studies.

Mutagenicity

The genotoxic potential of denosumab has not been evaluated.

Impairment of Fertility

Denosumab had no effect on female fertility or male reproductive organs in monkeys at doses that were 6.5-to 25-fold higher than the recommended human dose of 120 mg subcutaneously administered once every 4 weeks, based on body weight (mg/kg).

13.2 Animal Toxicology and/or Pharmacology

Denosumab products are inhibitors of osteoclastic bone resorption via inhibition of RANKL.

Because the biological activity of denosumab in animals is specific to nonhuman primates, evaluation of genetically engineered (knockout) mice or use of other biological inhibitors of the RANK/RANKL pathway, OPG-Fc and RANK-Fc, provided additional information on the pharmacodynamic properties of denosumab. RANK/RANKL knockout mice exhibited absence of lymph node formation, as well as an absence of lactation due to inhibition of mammary gland maturation (lobulo-alveolar gland development during pregnancy). Neonatal RANK/RANKL knockout mice exhibited reduced bone growth and lack of tooth eruption. A corroborative study in 2-week-old rats given the RANKL inhibitor OPG-Fc also showed reduced bone growth, altered growth plates, and impaired tooth eruption. These changes were partially reversible in this model when dosing with the RANKL inhibitors was discontinued.

14 CLINICAL TRIALS

14.1 Bone Metastasis from Solid Tumors

The safety and efficacy of denosumab for the prevention of skeletal-related events in patients with bone metastases from solid tumors was demonstrated in three international, randomized (1:1), double-blind, active-controlled, noninferiority trials comparing denosumab with zoledronic acid. In all three trials, patients were randomized to receive 120 mg denosumab subcutaneously every 4 weeks or 4 mg zoledronic acid intravenously (IV) every 4 weeks (dose adjusted for reduced renal function). Patients with creatinine clearance less than 30 mL/min were excluded. In each trial, the main outcome measure was demonstration of noninferiority of time to first skeletal-related event (SRE) as compared to zoledronic acid. Supportive outcome measures were superiority of time to first SRE and superiority of time to first and subsequent SRE; testing for these outcome measures occurred if the main outcome measure was statistically significant. An SRE was defined as any of the following: pathologic fracture, radiation therapy to bone, surgery to bone, or spinal cord compression.

Study 20050136 (NCT00321464) enrolled 2046 patients with advanced breast cancer and bone metastasis. Randomization was stratified by a history of prior SRE (yes or no), receipt of chemotherapy within 6 weeks prior to randomization (yes or no), prior oral bisphosphonate use (yes or no), and region (Japan or other countries). Forty percent of patients had a previous SRE, 40% received chemotherapy within 6 weeks prior to randomization, 5% received prior oral bisphosphonates, and 7% were enrolled from Japan. Median age was 57 years, 80% of patients were White, and 99% of patients were women. The median number of doses administered was 18 for denosumab and 17 for zoledronic acid.

Study 20050244 (NCT00330759) enrolled 1776 adults with solid tumors other than breast and castrate-resistant prostate cancer with bone metastasis and multiple myeloma. Randomization was stratified by previous SRE (yes or no), systemic anticancer therapy at time of randomization (yes or no), and tumor type (non-small cell lung cancer, myeloma, or other). Eighty-seven percent were receiving systemic anticancer therapy at the time of randomization, 52% had a previous SRE, 64% of patients were men, 87% were White, and the median age was 60 years. A total of 40% of patients had non-small cell lung cancer, 10% had multiple myeloma, 9% had renal cell carcinoma, and 6% had small cell lung cancer. Other tumor types each comprised less than 5% of the enrolled population. The median number of doses administered was 7 for both denosumab and zoledronic acid.

Study 20050103 (NCT00321620) enrolled 1901 men with castrate-resistant prostate cancer and bone metastasis. Randomization was stratified by previous SRE, PSA level (less than 10 ng/mL or 10 ng/mL or greater) and receipt of chemotherapy within 6 weeks prior to randomization (yes or no). Twenty-six percent of patients had a previous SRE, 15% of patients had PSA less than 10 ng/mL, and 14% received chemotherapy within 6 weeks prior to randomization. Median age was 71 years and 86% of patients were White. The median number of doses administered was 13 for denosumab and 11 for zoledronic acid.

Denosumab delayed the time to first SRE following randomization as compared to zoledronic acid in patients with breast or castrate-resistant prostate cancer (CRPC) with osseous metastases (Table 2). In patients with bone metastasis due to other solid tumors or lytic lesions due to multiple myeloma, denosumab was noninferior to zoledronic acid in delaying the time to first SRE following randomization.

Overall survival and progression-free survival were similar between arms in all three trials.

Table 2. Efficacy Results for Denosumab Compared to Zoledronic Acid

 | Study 20050136 Metastatic Breast Cancer |  | Study 20050244 Metastatic Solid Tumors or Multiple Myeloma |  | Study 20050103 Metastatic CRPCa
 | Denosumab N = 1026 | Zoledronic Acid; N = 1020 | Denosumab N = 886 | Zoledronic Acid; N = 890 | Denosumab N = 950 | Zoledronic Acid; N = 951
First On-study SRE
Number of Patients who had SREs (%) | 315 (30.7) | 372 (36.5) | 278 (31.4) | 323 (36.3) | 341 (35.9) | 386 (40.6)
Components of First SRE
Radiation to Bone | 82 (8.0) | 119 (11.7) | 119 (13.4) | 144 (16.2) | 177 (18.6) | 203 (21.3)
Pathological Fracture | 212 (20.7) | 238 (23.3) | 122 (13.8) | 139 (15.6) | 137 (14.4) | 143 (15.0)
Surgery to Bone | 12 (1.2) | 8 (0.8) | 13 (1.5) | 19 (2.1) | 1 (0.1) | 4 (0.4)
Spinal Cord Compression | 9 (0.9) | 7 (0.7) | 24 (2.7) | 21 (2.4) | 26 (2.7) | 36 (3.8)
Median Time to SRE (months) | NRb | 26.4 | 20.5 | 16.3 | 20.7 | 17.1
Hazard Ratio (95% CI) | 0.82 (0.71, 0.95) |  | 0.84 (0.71, 0.98) |  | 0.82 (0.71, 0.95)
Noninferiority p-value | < 0.001 |  | < 0.001 |  | < 0.001
Superiority p-valuec | 0.010 |  | 0.060 |  | 0.008
First and Subsequent SREd
Mean Number/Patient | 0.46 | 0.60 | 0.44 | 0.49 | 0.52 | 0.61
Rate Ratio (95% CI) | 0.77 (0.66, 0.89) |  | 0.90 (0.77, 1.04) |  | 0.82 (0.71, 0.94)
Superiority p-valuee | 0.001 |  | 0.145 |  | 0.009

a CRPC = castrate-resistant prostate cancer.

b NR = not reached.

c Superiority testing performed only after denosumab demonstrated to be noninferior to zoledronic acid within trial.

d All skeletal events postrandomization; new events defined by occurrence ≥ 21 days after preceding event.

e Adjusted p-values are presented.

14.2 Multiple Myeloma

The efficacy of denosumab for the prevention of skeletal-related events in newly diagnosed multiple myeloma patients with treatment through disease progression, was evaluated in Study 20090482 (NCT01345019), an international, randomized (1:1), double-blind, active-controlled, noninferiority trial comparing denosumab with zoledronic acid. In this trial, patients were randomized to receive 120 mg denosumab subcutaneously every 4 weeks or 4 mg zoledronic acid intravenously (IV) every 4 weeks (dose adjusted for reduced renal function). Patients with creatinine clearance less than 30 mL/min were excluded. In this trial, the main efficacy outcome measure was noninferiority of time to first skeletal-related event (SRE). Additional efficacy outcome measures were superiority of time to first SRE, time to first and subsequent SRE, and overall survival. An SRE was defined as any of the following: pathologic fracture, radiation therapy to bone, surgery to bone, or spinal cord compression.

Study 20090482 enrolled 1718 newly diagnosed multiple myeloma patients with bone lesions. Randomization was stratified by a history of prior SRE (yes or no), the anti-myeloma agent being utilized/planned to be utilized in first-line therapy (novel therapy-based or non-novel therapy-based [novel therapies include bortezomib, lenalidomide, or thalidomide]), intent to undergo autologous PBSC transplantation (yes or no), stage at diagnosis (International Staging System I or II or III) and region Japan (yes or no). At study enrollment, 96% of the patients were receiving or planning to receive novel therapy-based first-line anti-myeloma therapy, 55% of the patients intended to undergo autologous PBSC transplantation, 61% of patients had a previous SRE, 32% were at ISS Stage I, 38% were at ISS Stage II and 29% were at ISS Stage III, and 2% were enrolled from Japan. Median age was 63 years, 82% of patients were White, and 46% of patients were women. The median number of doses administered was 16 for denosumab and 15 for zoledronic acid.

Denosumab was noninferior to zoledronic acid in delaying the time to first SRE following randomization (HR = 0.98, 95% CI, 0.85 to 1.14). The results for overall survival (OS) were comparable between denosumab and zoledronic acid treatment groups with a hazard ratio of 0.90 (95% CI: 0.70, 1.16).

Table 3. Efficacy Results for Denosumab Compared to Zoledronic Acid

 | Study 20090482 Multiple Myeloma
 | Denosumab; N = 859 | Zoledronic Acid; N = 859
First On-study SRE
Number of Patients who had SREs (%) | 376 (43.8) | 383 (44.6)
Components of First SRE
Radiation to Bone | 47 (5.5) | 62 (7.2)
Pathological Fracture | 342 (39.8) | 338 (39.3)
Surgery to Bone | 37 (4.3) | 48 (5.6)
Spinal Cord Compression | 6 (0.7) | 4 (0.5)
Median Time to SRE (months); (95% CI) | 22.8; (14.7, NEa) | 24; (16.6, 33.3)
Hazard Ratio (95% CI) | 0.98 (0.85, 1.14)

a NE = not estimable

14.3 Giant Cell Tumor of Bone

The safety and efficacy of denosumab for the treatment of giant cell tumor of bone in adults or skeletally mature adolescents were demonstrated in two open-label trials [Study 20040215 (NCT00396279) and Study 20062004 (NCT00680992)] that enrolled patients with histologically confirmed measurable giant cell tumor of bone that was either recurrent, unresectable, or for which planned surgery was likely to result in severe morbidity. Patients received 120 mg denosumab subcutaneously every 4 weeks with a loading dose on Days 8 and 15 of the first cycle of therapy. Patients who discontinued denosumab then entered the safety follow-up phase for a minimum of 60 months. Retreatment with denosumab while in safety follow-up was allowed for patients who initially demonstrated a response to denosumab (e.g., in the case of recurrent disease).

Study 20040215 was a single-arm, pharmacodynamic, and proof of concept trial conducted in 37 adult patients with unresectable or recurrent giant cell tumor of bone. Patients were required to have histologically confirmed giant cell tumor of bone and radiologic evidence of measurable disease from a computed tomography (CT) or magnetic resonance imaging (MRI) obtained within 28 days prior to study enrollment. Patients enrolled in Study 20040215 underwent CT or MRI assessment of giant cell tumor of bone at baseline and quarterly during denosumab treatment.

Study 20062004 was a parallel-cohort, proof of concept, and safety trial conducted in 535 adult or skeletally mature adolescent patients with histologically confirmed giant cell tumor of bone and evidence of measurable active disease. Study 20062004 enrolled 19 patients who were 12 to 16 years of age [see Use in Specific Populations (8.4)]. Patients enrolled into one of three cohorts: Cohort 1 enrolled 268 patients with surgically unsalvageable disease (e.g., sacral or spinal sites of disease, or pulmonary metastases); Cohort 2 enrolled 252 patients with surgically salvageable disease where the investigator determined that the planned surgery was likely to result in severe morbidity (e.g., joint resection, limb amputation, or hemipelvectomy); Cohort 3 enrolled 15 patients who previously participated in Study 20040215. Patients underwent imaging assessment of disease status at intervals determined by their treating physician.

A retrospective interim analysis concluded by an independent review committee evaluated objective response in 187 patients enrolled and treated in Study 20040215 and Study 20062004 for whom baseline and at least one post-baseline radiographic assessment were available (27 of 37 patients enrolled in Study 20040215 and 160 of 270 patients enrolled in Cohorts 1 and 2 of Study 20062004). The primary efficacy outcome measure was objective response rate using Response Evaluation Criteria in Solid Tumors (RECIST) v1.1.

The overall objective response rate (RECIST 1.1) was 25% (95% CI: 19, 32). All responses were partial responses. The estimated median time to response was 3 months. In the 47 patients with an objective response, the median duration of follow-up was 20 months (range: 2 to 44 months), and 51% (24/47) had a duration of response lasting at least 8 months. Three patients experienced disease progression following an objective response.

14.4 Hypercalcemia of Malignancy

The safety and efficacy of denosumab was demonstrated in an open-label, single-arm trial [Study 20070315 (NCT00896454)] that enrolled 33 patients with hypercalcemia of malignancy (with or without bone metastases) refractory to treatment with intravenous bisphosphonate therapy. Patients received denosumab subcutaneously every 4 weeks with additional 120 mg doses on Days 8 and 15 of the first month of therapy.

In this trial, refractory hypercalcemia of malignancy was defined as an albumin-corrected calcium of > 12.5 mg/dL (3.1 mmol/L) despite treatment with intravenous bisphosphonate therapy in 7 to 30 days prior to initiation of denosumab therapy. The primary outcome measure was the proportion of patients achieving a response, defined as corrected serum calcium (CSC) ≤ 11.5 mg/dL (2.9 mmol/L), within 10 days after denosumab administration. Efficacy data are summarized in Figure 1 and Table 4. Concurrent chemotherapy did not appear to affect response to denosumab.

Figure 1. Corrected Serum Calcium by Visit in Responders (Median and Interquartile Range)

N= Number of responders who received ≥ 1 dose of investigational product

n = Number of responders who had no missing data at baseline and the time point of interest

Table 4. Efficacy in Patients with Hypercalcemia of Malignancy Refractory to Bisphosphonate Therapy

 | N = 33 | Proportion (%); (95% CI)
All Responders (CSC ≤ 11.5 mg/dL) by Day 10 | 21 | 63.6; (45.1, 79.6)
All Responders by Day 57 | 23 | 69.7; (51.3, 84.4)
Complete Responders (CSC ≤ 10.8 mg/dL) by Day 10 | 12 | 36.4; (20.4, 54.9)
All Complete Responders by Day 57 | 21 | 63.6; (45.1, 79.6)

Median time to response (CSC ≤ 11.5 mg/dL) was 9 days (95% CI: 8, 19), and the median duration of response was 104 days (95% CI: 7, not estimable). Median time to complete response (CSC ≤ 10.8 mg/dL) was 23 days (95% CI: 9, 36), and the median duration of complete response was 34 days (95% CI: 1, 134).

16 HOW SUPPLIED

How Supplied

Oziltus (denosumab-mobz) injection is a clear, colorless to pale yellow solution supplied in a single-dose vial.

120 mg/1.7 mL (70 mg/mL) | 1 vial per carton | NDC 70121-2701-1

Storage and Handling

Store Oziltus refrigerated at 2°C to 8°C (36°F to 46°F) in the original carton to protect from light. Do not freeze. Prior to administration, Oziltus may be allowed to reach room temperature up to 25°C (77°F) in the original container. Once removed from the refrigerator, Oziltus must not be exposed to temperatures above 25°C (77°F) and must be used within 14 days. Discard Oziltus if not used within the 14 days. Do not use Oziltus after the expiry date printed on the label.

17 PATIENT COUNSELING INFORMATION

Drug Products with Same Active Ingredient

Advise patients that if they receive Oziltus, they should not receive other denosumab products concomitantly [see Warnings and Precautions (5.1)].

Hypersensitivity

Advise patients to seek prompt medical attention if signs or symptoms of hypersensitivity reactions occur. Advise patients who have had signs or symptoms of systemic hypersensitivity reactions that they should not receive denosumab products [see Warnings and Precautions (5.2) and Contraindications (4.2)].

Hypocalcemia

Adequately supplement patients with calcium and vitamin D and instruct them on the importance of maintaining serum calcium levels while receiving Oziltus [see Warnings and Precautions (5.3) and Use in Specific Populations (8.6)]. Advise patients to seek prompt medical attention if they develop signs or symptoms of hypocalcemia.

Osteonecrosis of the Jaw

Advise patients to maintain good oral hygiene during treatment with Oziltus and to inform their dentist prior to dental procedures that they are receiving Oziltus. Patients should avoid invasive dental procedures during treatment with Oziltus and inform their healthcare provider or dentist if they experience persistent pain and/or slow healing of the mouth or jaw after dental surgery [see Warnings and Precautions (5.4)].

Atypical Subtrochanteric and Diaphyseal Femoral Fracture

Advise patients to report new or unusual thigh, hip, or groin pain [see Warnings and Precautions (5.5)].

Hypercalcemia Following Treatment Discontinuation in Patients with Giant Cell Tumor of Bone and in Patients with Growing Skeletons

Advise patients to report nausea, vomiting, headache, and decreased alertness following treatment discontinuation [see Warnings and Precautions (5.6) and Use in Specific Populations (8.4)].

Multiple Vertebral Fractures (MVF) Following Treatment Discontinuation

Advise patients that after treatment with Oziltus is stopped there may be an increased risk of having broken bones in the spine especially in patients who have had a fracture or who have had osteoporosis.

Advise patients not to interrupt Oziltus therapy without their physician’s advice [see Warnings and Precautions (5.7)].

Embryo-Fetal Toxicity

Advise females of reproductive potential that Oziltus can cause harm to a fetus and to inform their healthcare provider of a known or suspected pregnancy [see Warnings and Precautions (5.8) and Use in Specific Populations (8.1, 8.3)].

Advise females of reproductive potential to use effective contraception during treatment and for at least 5 months after the last dose of Oziltus [see Use in Specific Populations (8.3)].

Oziltus® (denosumab)

Manufactured by:

Amneal Pharmaceuticals LLC

Piscataway, NJ 08854

Product of Spain

US License No. 2241